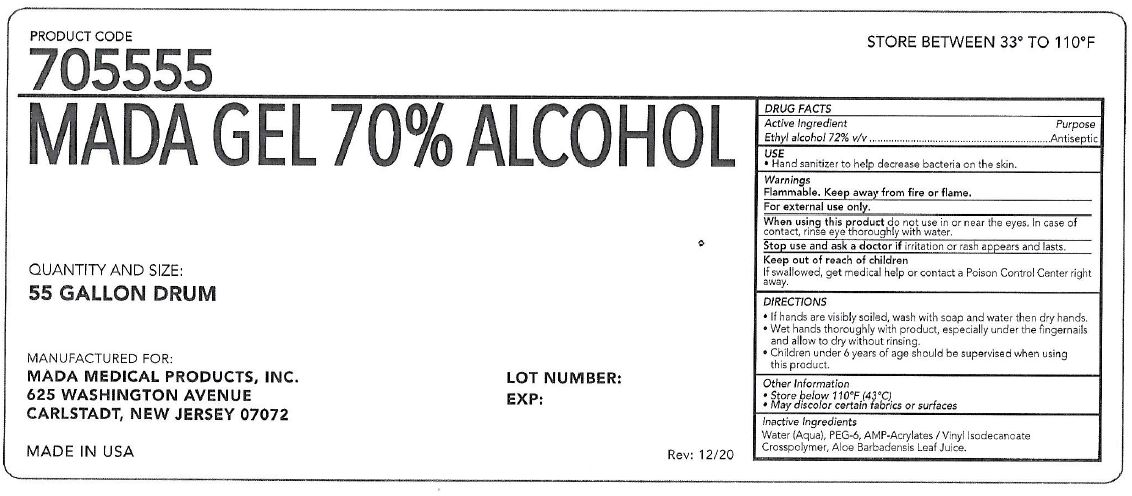 DRUG LABEL: MADA 70% ALCOHOL
NDC: 11928-006 | Form: GEL
Manufacturer: Mada Medical Products, Inc.
Category: otc | Type: HUMAN OTC DRUG LABEL
Date: 20201202

ACTIVE INGREDIENTS: ALCOHOL 72 L/100 L
INACTIVE INGREDIENTS: ACRYLATES/VINYL ISODECANOATE CROSSPOLYMER (10000 MPA.S NEUTRALIZED AT 0.5%); WATER; ALOE VERA LEAF; POLYETHYLENE GLYCOL 300

Active Ingredient

Ethyl alcohol 72% v/v

Purpose

Antiseptic

USE

Hand sanitizer to help decrease bacteria on the skin.

Warnings

Flammable. Keep away from fire or flame.

For external use only.

When using this product do not use in or near the eyes. In case of contact, rinse eye thoroughly with water.

Stop use and ask a doctor if irritation or rash appears and lasts.

Keep out of reach of children

If swallowed, get medical help or contact a Poison Control Center right away.

DIRECTIONS

- If hands are visibly soiled, wash with soap and water then dry hands.
- Wet hands thoroughly with product, especially under the fingernails and allow to dry without rinsing.
- Children under 6 years of age should be supervised when using this product.

Other Information

- Store below 110F (43C)
- May discolor certain fabrics or surfaces

Unactive Ingredients

Water (Aqua), PEG-6, AMP-Acrylates/Vinyl Isodecanoate Crosspolymer, Aloe Barbadensis Leaf Juice.

PACKAGE LABEL

PRODUCT CODE

705555

STORE BETWEEN 33 TO 110F

MADA GEL 70% ALCOHOL

QUANTITY AND SIZE:

55 GALLON DRUM

MANUFACTURED FOR:

MADA MEDICAL PRODUCTS, INC.

625 WASHINGTON AVENUE

CARLSTADT, NEW JERSEY 07072

MADE IN USA

LOT NUMBER:

EXP:

Rev:12/20